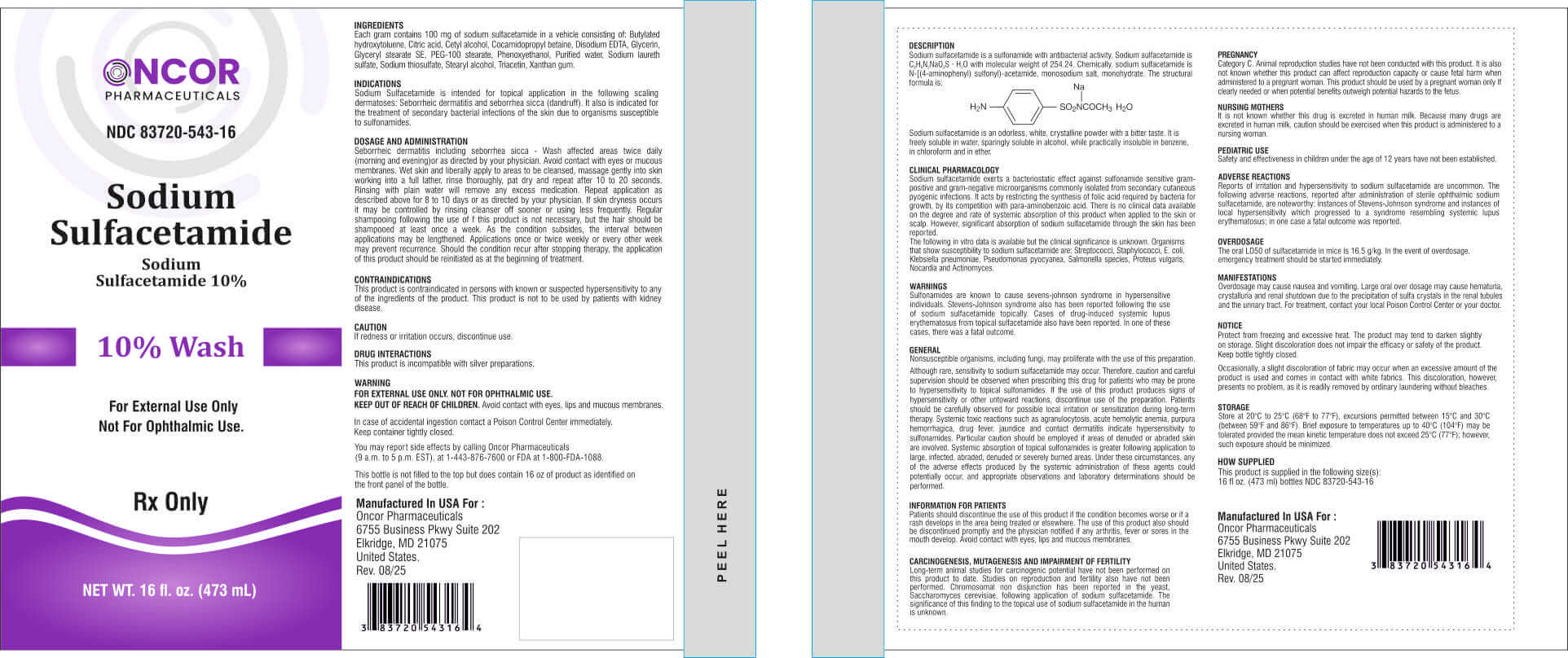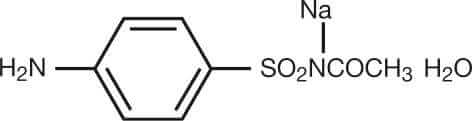 DRUG LABEL: Sodium Sulfacetamide 10% wash
NDC: 83720-543 | Form: LIQUID
Manufacturer: Oncor Pharmaceuticals
Category: prescription | Type: HUMAN PRESCRIPTION DRUG LABEL
Date: 20260211

ACTIVE INGREDIENTS: SULFACETAMIDE SODIUM 100 mg/1 mL
INACTIVE INGREDIENTS: BUTYLATED HYDROXYTOLUENE; CITRIC ACID; CETYL ALCOHOL; COCAMIDOPROPYL BETAINE; EDETATE DISODIUM; GLYCERIN; GLYCERYL STEARATE SE; PEG-100 STEARATE; PHENOXYETHANOL; WATER; SODIUM LAURETH SULFATE; SODIUM THIOSULFATE; STEARYL ALCOHOL; TRIACETIN; XANTHAN GUM

Sodium Sulfacetamide 10% Wash

Rx Only For External Use Only Not For Ophthalmic Use. DESCRIPTION

Each gram contains 100 mg of sodium sulfacetamide in a vehicle consisting of: Butylated hydroxytoluene, Citric acid, Cetyl alcohol, Cocamidopropyl betaine, Disodium EDTA, Glycerin, Glyceryl stearate SE, PEG-100 stearate, Phenoxyethanol, Purified water, Sodium laureth sulfate, Sodium thiosulfate, Stearyl alcohol, Triacetin, Xanthan gum.

Sodium sulfacetamide is a sulfonamide with antibacterial activity. Sodium sulfacetamide is C8H9N2NaO3S · H2O with molecular weight of 254.24. Chemically. sodium sulfacetamide is N-[(4-aminophenyl) sulfonyl)-acetamide, monosodium salt, monohydrate. The structural formula is:

Sodium sulfacetamide is an odorless, white, crystalline powder with a bitter taste. It is freely soluble in water, sparingly soluble in alcohol, while practically insoluble in benzene, in chloroform and in ether.

INDICATIONS

Sodium Sulfacetamide is intended for topical application in the following scaling dermatoses: Seborrheic dermatitis and seborrhea sicca (dandruff). It also is indicated for the treatment of secondary bacterial infections of the skin due to organisms susceptible to sulfonamides.

DOSAGE AND ADMINISTRATION

Seborrheic dermatitis including seborrhea sicca - Wash affected areas twice daily (morning and evening)or as directed by your physician. Avoid contact with eyes or mucous membranes. Wet skin and liberally apply to areas to be cleansed, massage gently into skin working into a full lather, rinse thoroughly, pat dry and repeat after 10 to 20 seconds. Rinsing with plain water will remove any excess medication. Repeat application as described above for 8 to 10 days or as directed by your physician. If skin dryness occurs it may be controlled by rinsing cleanser off sooner or using less frequently. Regular shampooing following the use of f this product is not necessary, but the hair should be shampooed at least once a week. As the condition subsides, the interval between applications may be lengthened. Applications once or twice weekly or every other week may prevent recurrence. Should the condition recur after stopping therapy, the application of this product should be reinitiated as at the beginning of treatment.

CONTRAINDICATIONS

This product is contraindicated in persons with known or suspected hypersensitivity to any of the ingredients of the product. This product is not to be used by patients with kidney disease.

CAUTION

If redness or irritation occurs, discontinue use.

DRUG INTERACTIONS

This product is incompatible with silver preparations.

WARNING

FOR EXTERNAL USE ONLY. NOT FOR OPHTHALMIC USE.
KEEP OUT OF REACH OF CHILDREN.Avoid contact with eyes, lips and mucous membranes.

Sulfonamides are known to cause sevens-johnson syndrome in hypersensitive individuals. Stevens-Johnson syndrome also has been reported following the use of sodium sulfacetamide topica ly. Cases of drug-induced systemic lupus erythematosus from topical sulfacetamide also have been reported. In one of these cases, there was a fatal outcome.

CLINICAL PHARMACOLOGY

Sodium sulfacetamide exerts a bacteriostatic effect against sulfonamide sensitive gram positive and gram-negative microorganisms commonly isolated from secondary cutaneous pyogenic infections. It acts by restricting the synthesis of folic acid required by bacteria for growth, by its competition with para-aminobenzoic acid. There is no clinical data available on the degree and rate of systemic absorption of this product when applied to the skin or scalp. However, significant absorption of sodium sulfacetamide through the skin has been reported.

The fo lowing in vitro data is available but the clinical signicance is unknown. Organisms that show susceptibility to sodium sulfacetamide are: Streptococci, Staphylococci, E. coli, Klebsie la pneumoniae, Pseudomonas pyocyanea, Salmone la species, Proteus vulgaris, Nocardia and Actinomyces.

GENERAL

Nonsusceptible organisms, including fungi, may proliferate with the use of this preparation.

Although rare, sensitivity to sodium sulfacetamide may occur. Therefore, caution and careful supervision should be observed when prescribing this drug for patients who may be prone to hypersensitivity to topical sulfonamides. If the use of this product produces signs of hypersensitivity or other untoward reactions, discontinue use of the preparation. Patients should be carefully observed for possible local irritation or sensitization during long-term therapy. Systemic toxic reactions such as agranulocytosis, acute hemolytic anemia, purpura hemorrhagica, drug fever, jaundice and contact dermatitis indicate hypersensitivity to sulfonamides. Particular caution should be employed if areas of denuded or abraded skin are involved. Systemic absorption of topical sulfonamides is greater following application to large, infected, abraded, denuded or severely burned areas. Under these circumstances, any of the adverse effects produced by the systemic administration of these agents could potentially occur, and appropriate observations and laboratory determinations should be performed.

INFORMATION FOR PATIENTS

Patients should discontinue the use of this product if the condition becomes worse or if a rash develops in the area being treated or elsewhere. The use of this product also should be discontinued promptly and the physician notified if any arthritis, fever or sores in the mouth develop. Avoid contact with eyes, lips and mucous membranes.

CARCINOGENESIS, MUTAGENESIS AND IMPAIRMENT OF FERTILITY

Long-term animal studies for carcinogenic potential have not been performed on this product to date. Studies on reproduction and fertility also have not been performed. Chromosomal non disjunction has been reported in the yeast, Saccharomyces cerevisiae, following application of sodium sulfacetamide. The significance of this finding to the topical use of sodium sulfacetamide in the human is unknown.

PREGNANCY

Category C. Animal reproduction studies have not been conducted with this product. It is also not known whether this product can affect reproduction capacity or cause fetal harm when administered to a pregnant woman. This product should be used by a pregnant woman only If
clearly needed or when potential benefits outweigh potential hazards to the fetus.

NURSING MOTHERS

It is not known whether this drug is excreted in human milk. Because many drugs are excreted in human milk, caution should be exercised when this product is administered to a nursing woman.

PEDIATRIC USE

Safety and effectiveness in children under the age of 12 years have not been established.

ADVERSE REACTIONS

Reports of irritation and hypersensitivity to sodium sulfacetamide are uncommon. The following adverse reactions, reported after administration of sterile ophthalmic sodium sulfacetamide, are noteworthy: instances of Stevens-Johnson syndrome and instances of local hypersensitivity which progressed to a syndrome resembling systemic lupus erythematosus; in one case a fatal outcome was reported.

OVERDOSAGE

The oral LD50 of sulfacetamide in mice is 16.5 g/kg. In the event of overdosage, emergency treatment should be started immediately.

Overdosage may cause nausea and vomiting. Large oral over dosage may cause hematuria, crystalluria and renal shutdown due to the precipitation of sulfa crystals in the renal tubules and the urinary tract. For treatment, contact your local Poison Control Center or your doctor.

NOTICE

Protect from freezing and excessive heat. The product may tend to darken slightly on storage. Slight discoloration does not impair the efcacy or safety of the product. Keep bottle tightly closed.

Occasionally, a slight discoloration of fabric may occur when an excessive amount of the product is used and comes in contact with white fabrics. This discoloration, however, presents no problem, as it is readily removed by ordinary laundering without bleaches.

STORAGE

Store at 20°C to 25°C (68°F to 77°F), excursions permitted between 15°C and 30°C (between 59°F and 86°F). Brief exposure to temperatures up to 40°C (104°F) may be tolerated provided the mean kinetic temperature does not exceed 25°C (77°F); however, such exposure should be minimized.

HOW SUPPLIED

This product is supplied in the following size(s):
16 fl oz. (473 ml) bottles NDC 83720-543-16

In case of accidental ingestion contact a Poison Control Center immediately. Keep container tightly closed.

You may report side effects by ca ling Oncor Pharmaceuticals (9 a.m. to 5 p.m. EST), at 1-443-876-7600 or FDA at 1-800-FDA-1088.

This bottle is not filled to the top but does contain 16 oz of product as identified on the front panel of the bottle.

PACKAGE LABEL

Manufactured In USA For :

Oncor Pharmaceuticals
6755 Business Pkwy Suite 202
Elkridge, MD 21075
United States.
Rev. 08/25